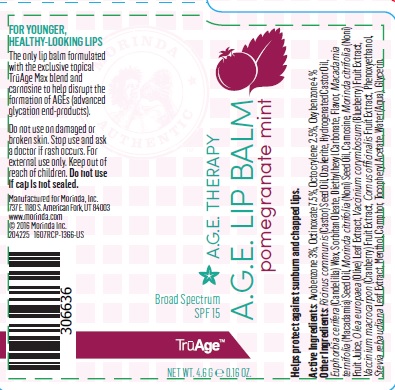 DRUG LABEL: TruAge Lip Balm Pomegranate Mint
NDC: 14743-337 | Form: LIPSTICK
Manufacturer: Tahitian Noni International
Category: otc | Type: HUMAN OTC DRUG LABEL
Date: 20201208

ACTIVE INGREDIENTS: Avobenzone 3 g/100 g; Octinoxate 7.5 g/100 g; OCTOCRYLENE 2.5 g/100 g; OXYBENZONE 4 g/100 g
INACTIVE INGREDIENTS: CAMPHOR (NATURAL); CARNOSINE; CORNUS OFFICINALIS FRUIT; CANDELILLA WAX; GLYCERIN; PEG-10 HYDROGENATED CASTOR OIL; MACADAMIA OIL; MENTHOL; MORINDA CITRIFOLIA SEED OIL; NONI FRUIT JUICE; OLEA EUROPAEA FLOWER; CERESIN; PHENOXYETHANOL; RICINUS COMMUNIS SEED; PEG-6 SORBITAN OLEATE; STEVIA REBAUDIANA WHOLE; .ALPHA.-TOCOPHEROL ACETATE; VACCINIUM CORYMBOSUM WHOLE; VACCINIUM MACROCARPON WHOLE; WATER

A.G.E. Therapy Lip Balm SPF 15 Pomegranate Mint

Active Ingredients

Avobenzone 3%

Octinoxate 7.5%

Octocrylene 2.5%

Oxybenzone 4%

INDICATIONS AND USAGE

Helps protect against sunburn and chapped lips

Other Ingredients

Camphor, Carnosine, Cornus Officinalis Fruit Extract, Diethylhexyl Carbonate, Euphorbia Cerifera (Candelilla) Wax, Flavor, Glycerin, Hydrogenated Castor Oil, Macadamia Ternifolia Seed Oil, Menthol, Morinda Citrifolia Fruit Juice, Morinda Citrifolia L. (Noni) Seed Oil, Olea Europaea (Olive) Leaf Extract, Ozokerite, Phenoxyethanol, Ricinus Communis (Castor) Seed Oil, Sorbitan Oleate, Stevia Rebaudiana Leaf/Stem Extract, Tocopheryl Acetate, Vaccinium Corymbosum (Blueberry) Fruit Extract, Vaccinium Macrocarpon (Cranberry) Fruit Extract, Water

WARNINGS

DO NOT USE

Do not used on damaged or broken skin. Do not use if cap is not sealed.

Stop use and ask a doctor if rash occurs.

Keep out of reach of children.